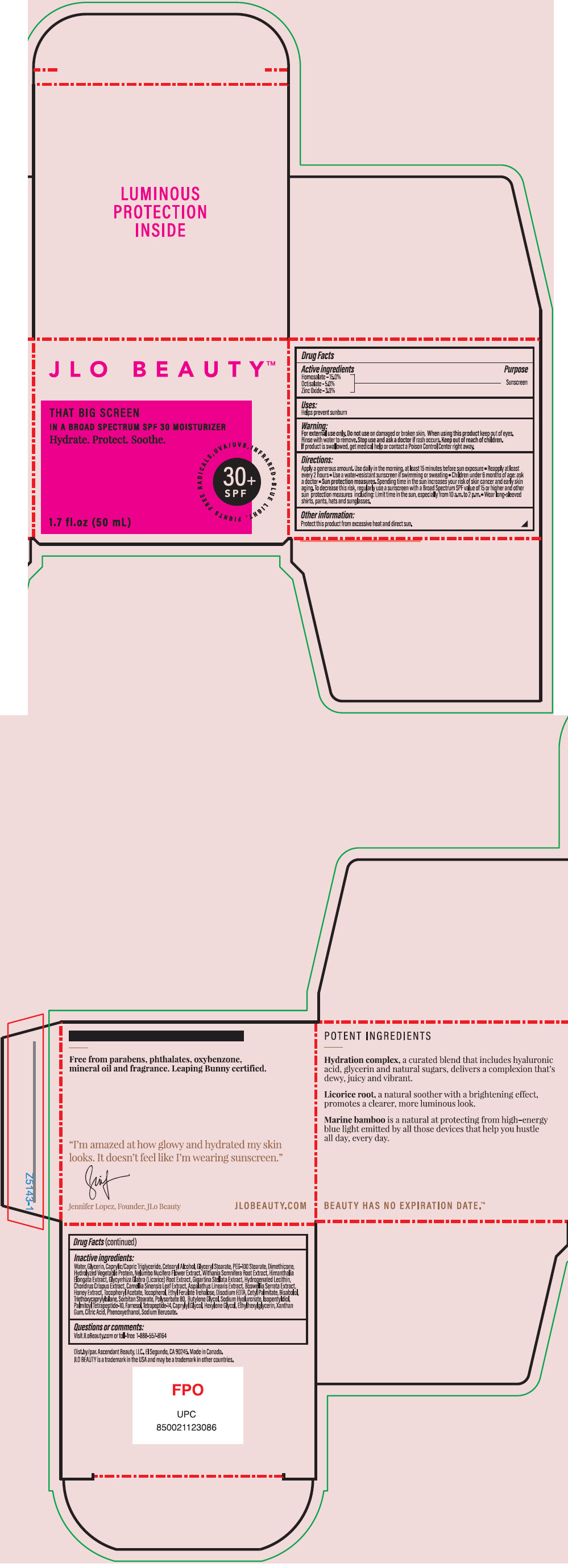 DRUG LABEL: JLo Beauty That Big Screen Broad Spectrum SPF 30 Moisturizer
NDC: 79625-001 | Form: CREAM
Manufacturer: Ascendant Beauty LLC
Category: otc | Type: HUMAN OTC DRUG LABEL
Date: 20231221

ACTIVE INGREDIENTS: Homosalate 150 mg/1 mL; Octisalate 50 mg/1 mL; Zinc Oxide 30 mg/1 mL
INACTIVE INGREDIENTS: Water; Glycerin; MEDIUM-CHAIN TRIGLYCERIDES; CETOSTEARYL ALCOHOL; GLYCERYL MONOSTEARATE; PEG-100 Stearate; Dimethicone; NELUMBO NUCIFERA FLOWER; WITHANIA SOMNIFERA ROOT; HIMANTHALIA ELONGATA; GLYCYRRHIZA GLABRA; MASTOCARPUS STELLATUS; HYDROGENATED SOYBEAN LECITHIN; CHONDRUS CRISPUS CARRAGEENAN; GREEN TEA LEAF; INDIAN FRANKINCENSE; HONEY; .ALPHA.-TOCOPHEROL ACETATE; Tocopherol; ETHYL FERULATE; TREHALOSE; EDETATE DISODIUM ANHYDROUS; Cetyl Palmitate; LEVOMENOL; Triethoxycaprylylsilane; SORBITAN MONOSTEARATE; Polysorbate 80; Butylene Glycol; HYALURONATE SODIUM; Isopentyldiol; Palmitoyl Tetrapeptide-10; Farnesol; Caprylyl Glycol; Hexylene Glycol; Ethylhexylglycerin; Xanthan Gum; CITRIC ACID MONOHYDRATE; Phenoxyethanol; Sodium Benzoate

JLo Beauty™ That Big Screen Broad Spectrum SPF 30 Moisturizer

Drug Fact Label

Active ingredient

Homosalate - 15.0%
Octisalate – 5.0%
Zinc – 3.0%

Purpose

Sunscreen

Use

Helps prevent sunburn.

Warnings

For external use only. Do not use on damaged or broken skin.

When using this product keep out of eyes. Rinse with water to remove.

Stop use and ask a doctor if rash occurs.

Keep out of reach of children. If product is swallowed, get medical help or contact a Poison Control Center right away.

Directions

Apply a generous amount. Use daily in the morning. At least 15 minutes before sun exposure

- Reapply at least every 2 hours
- Use a water-resistant sunscreen if swimming or sweating
- Children under 6 months of age: ask a doctor
- Sun protection measures, Spending time in the sun increases your risk, regularly use a sunscreen with a Broad Spectrum SPF value of 15 or higher and other sun protection measures including: Limit in the sun, especially from 10 a.am. to 2 p.m.
- Wear long0sleeved shirts, pants, hats and sunglasses.

Other information

Protect this product from excessive heat and direct sun.

Active Ingredients

Homosalate – 15.0%, Octisalate - 5.0%, Zinc Oxide - 3.0%

Inactive Ingredients

Water, Glycerin, Caprylic/Capric Triglyceride, Cetearyl Alcohol, Glyceryl Stearate, PEG-100 Stearate, Dimethicone, Hydrolyzed Vegetable Protein, Nelumbo Nucifera Flower Extract, Withania Somnifera Root Extract, Himanthalia Elongata Extract, Glycyrrhiza Glabra (Licorice) Root Extract, Gigartina Stellata Extract, Hydrogenated Lecithin, Chondrus Crispus Extract, Camellia Sinensis Leaf Extract, Aspalathus Linearis Extract, Boswellia Serrata Extract, Honey Extract, Tocopheryl Acetate, Tocopherol, Ethyl Ferulate Trehalose, Disodium EDTA, Cetyl Palmitate, Bisabolol, Triethoxycaprylylsilane, Sorbitan Stearate, Polysorbate 80, Butylene Glycol, Sodium Hyaluronate, Isopentyldiol, Palmitoyl Tetrapeptide-10, Farnesol, Tetrapeptide-14, Caprylyl Glycol, Hexylene Glycol, Ethylhexylglycerin, Xanthan Gum, Citric Acid, Phenoxyethanol, Sodium Benzoate.

Questions or comments?

Visit JLoBeauty.com or toll-free 1-800-557-8164

Dist.by/par. Ascendant Beauty, LLC., El Segundo, CA 90245.

PRINCIPAL DISPLAY PANEL - 50 mL Jar Box

JLO BEAUTY™

THAT BIG SCREEN
IN A BROAD SPECTRUM SPF 30 MOISTURIZER
Hydrate. Protect. Soothe.

FIGHTS FREE RADICALS, UVA/UVB, INFRARED + BLUE LIGHT.

30+
SPF

1.7 fl. oz (50 mL)